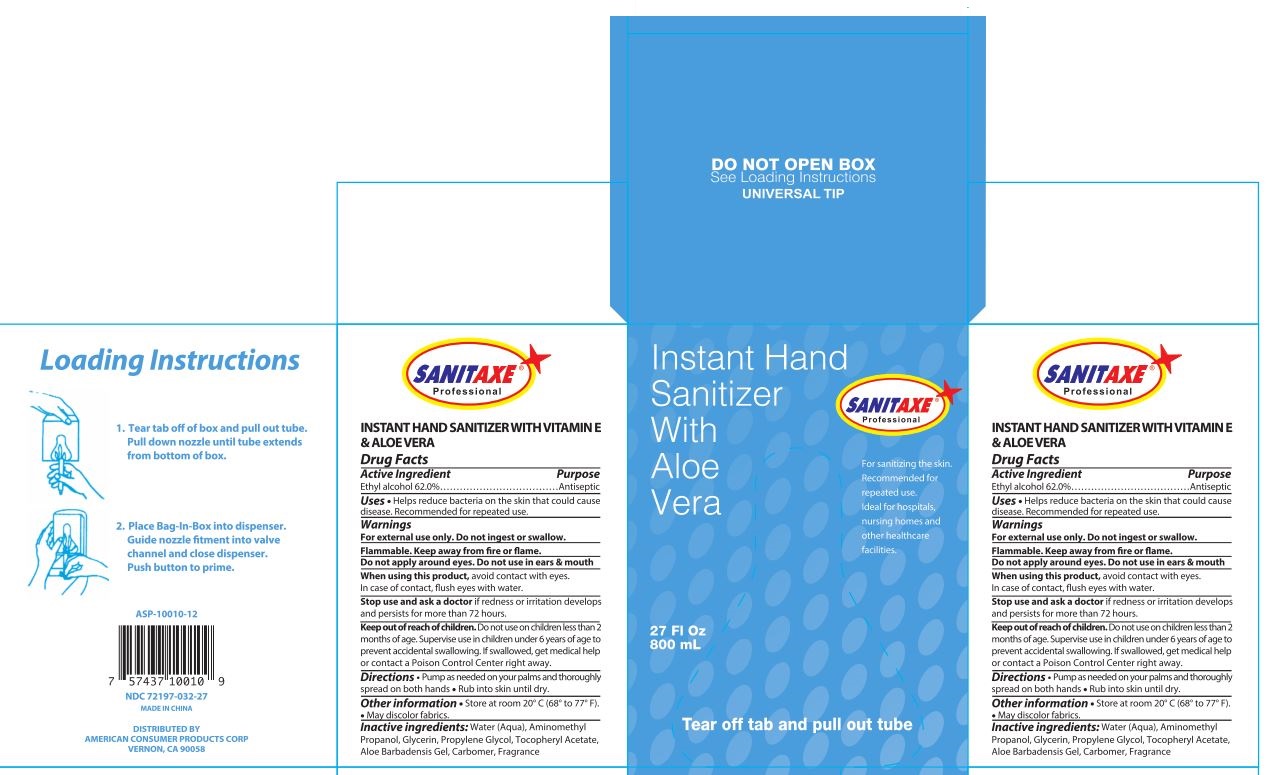 DRUG LABEL: SANITAXE 27 OZ INSTANT HAND SANITIZER WITH ALOE VERA
NDC: 72197-032 | Form: GEL
Manufacturer: American Consumer Products Corp
Category: otc | Type: HUMAN OTC DRUG LABEL
Date: 20250123

ACTIVE INGREDIENTS: ALCOHOL 62 mL/100 mL
INACTIVE INGREDIENTS: CARBOMER 934; WATER; GLYCERIN; PROPYLENE GLYCOL; ALPHA-TOCOPHEROL ACETATE; AMINOMETHYLPROPANOL; ALOE VERA LEAF

Sanitaxe Instant Hand Sanitizer

Active Ingredient

Ethyl alcohol 62%

Purpose

Antiseptic

Uses

Uses ● Helps reduce bacteria on the skin that could cause disease. Recommended for repeated use.

Warnings

Warnings – For external use only. Do not ingest or swallow.

Flammable. Keep away from fire or flame.

Do not apply around eyes. Do not use in ears & mouth.

When using this product, avoid contact with eyes. In case of contact, flush eyes with water.

Stop use and ask a doctor if redness or irritation develops and persists for more than 72 hours.

Keep out of reach of children. Do not use on children less than 2 months of age.

Supervise use in children under 6 years of age to prevent accidental swallowing.

If swallowed, get medical help or contact a Poison Control Center right away.

Directions

Directions ● pump as needed on your palms and thoroughly spread on both hands

● rub into skin until dry.

Other information

Other information ● store at room 20° C (68° to 77° F) ● may discolor fabrics.

Inactive ingredients

Inactive ingredients: Water (Aqua), Aminomethyl Propanol, Glycerin, Propylene Glycol, Tocopheryl Acetate, Aloe Barbadensis Gel, Carbomer, Fragrance